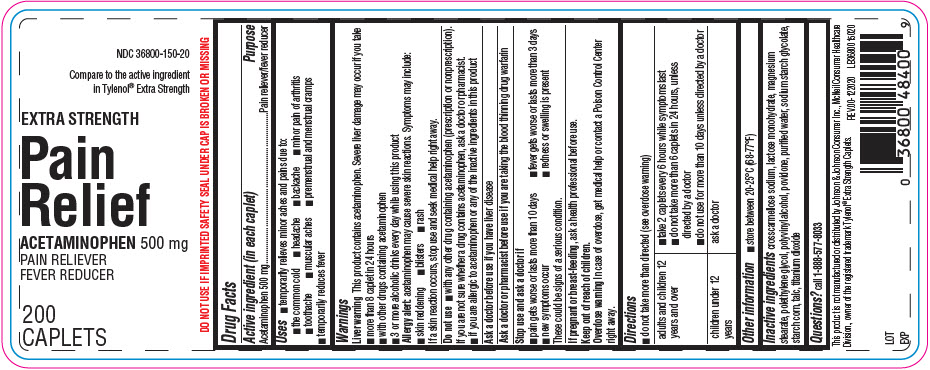 DRUG LABEL: Pain Relief Extra Strength
NDC: 36800-961 | Form: TABLET, COATED
Manufacturer: TOPCO ASSOCIATES LLC
Category: otc | Type: HUMAN OTC DRUG LABEL
Date: 20210308

ACTIVE INGREDIENTS: Acetaminophen 500 mg/1 1
INACTIVE INGREDIENTS: CROSCARMELLOSE SODIUM; Lactose Monohydrate; Magnesium Stearate; POLYETHYLENE GLYCOL, UNSPECIFIED; POLYVINYL ALCOHOL, UNSPECIFIED; POVIDONE, UNSPECIFIED; WATER; SODIUM STARCH GLYCOLATE TYPE A; STARCH, CORN; Talc; Titanium Dioxide

Pain Relief Extra Strength

Drug Facts

Active ingredient (in each caplet)

Acetaminophen 500 mg

Purpose

Pain reliever/fever reducer

Uses

- temporarily relieves minor aches and pains due to:
  - the common cold
  - headache
  - backache
  - minor pain of arthritis
  - toothache
  - muscular aches
  - premenstrual and menstrual cramps
- temporarily reduces fever

Warnings

Liver warning

This product contains acetaminophen. Severe liver damage may occur if you take

- more than 8 caplet in 24 hours
- with other drugs containing acetaminophen
- 3 or more alcoholic drinks every day while using this product

Allergy alert: acetaminophen may cause severe skin reactions. Symptoms may include:

- skin reddening
- blisters
- rash

If a skin reaction occurs, stop use and seek medical help right away.

Do not use

- with any other drug containing acetaminophen (prescription or nonprescription). If you are not sure whether a drug contains acetaminophen, ask a doctor or pharmacist.
- if you are allergic to acetaminophen or any of the inactive ingredients in this product

Ask a doctor before use if you have liver disease

Ask a doctor or pharmacist before use if you are taking the blood thinning drug warfarin

Stop use and ask a doctor if

- pain gets worse or lasts more than 10 days
- fever gets worse or lasts more than 3 days
- new symptoms occur
- redness or swelling is present

These could be signs of a serious condition.

PREGNANCY OR BREAST FEEDING

If pregnant or breast-feeding, ask a health professional before use.

Keep out of reach of children.

Overdose warning

In case of overdose, get medical help or contact a Poison Control Center right away.

Directions

- do not take more than directed (see overdose warning)

adults and children 12 years and over | - take 2 caplets every 6 hours while symptoms last - do not take more than 6 caplets in 24 hours, unless directed by a doctor - do not use for more than 10 days unless directed by a doctor
children under 12 years | ask a doctor

Other information

- store between 20-25°C (68-77°F)

Inactive ingredients

crosscarmellose sodium, lactose monohydrate, magnesium stearate, polethylene glycol, polyvinyl alcohol, povidone, purified water, sodium starch glycolate, starch corn, talc, titanium dioxide

Questions?

call 1-888-577-8033

PRINCIPAL DISPLAY PANEL - 200 Caplet Bottle Label

NDC 36800-150-20

Compare to the active ingredient
in Tylenol® Extra Strength

EXTRA STRENGTH

Pain
Relief

ACETAMINOPHEN 500 mg
PAIN RELIEVER
FEVER REDUCER

200
CAPLETS